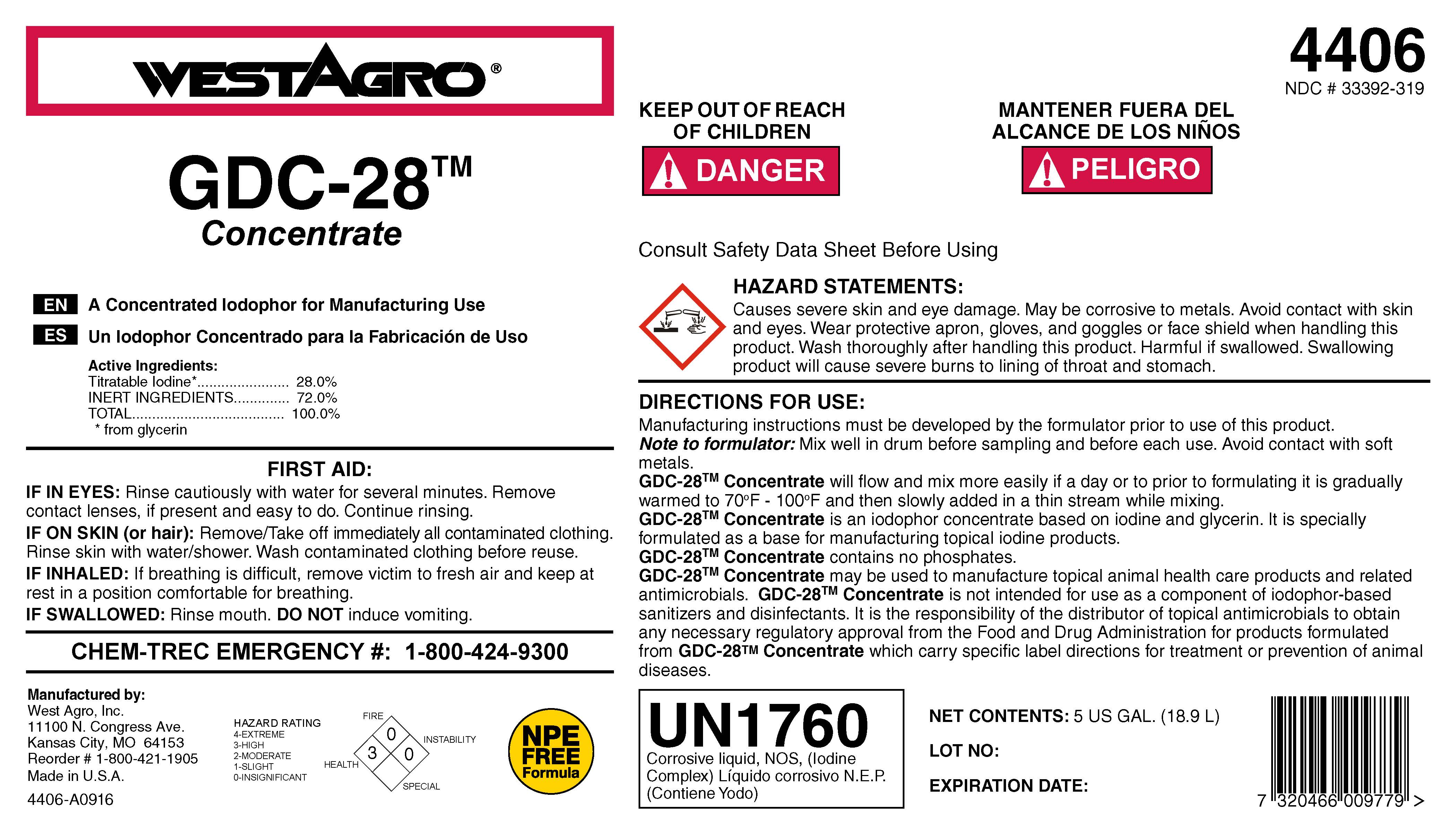 DRUG LABEL: GDC-28 Concentrate
NDC: 33392-319 | Form: SOLUTION, CONCENTRATE
Manufacturer: WestAgro, Inc.
Category: animal | Type: OTC ANIMAL DRUG LABEL
Date: 20211215

ACTIVE INGREDIENTS: IODINE 280 g/1 kg
INACTIVE INGREDIENTS: GLYCERIN; WATER; SODIUM IODIDE

WESTAGRO GDC-28TM Concentrate

EN A Concentrated Iodophor for Manufacturing Use

ES Un Iodophor concentrado para la Fabricacion de Uso

Active Ingredients:

Titratable Iodine* ...................28.0%

INERT INGREDIENTS ..............72.0%

TOTAL ..................................100.0%

* from glycerin

FIRST AID:

IF IN EYES: Rinse cautiously with water for several minutes. Remove contact lenses, if present and easy to do. Continue rinsing.

IF ON SKIN (or hair): Remove/Take off immediately all contaminated clothing. Rinse skin with water/shower. Wash contaminated clothing before reuse.

IF INHALED: If breathing is difficult, remove victim to fresh air and keep at rest in a position of comfortable breathing.

IF SWALLOWED: Rinse mouth. DO NOT induce vomiting.

CHEM-TREC EMERGENCY #: 1-800-424-9300

Manufactured by:

WestAgro, Inc.

11100 N. Congress Ave.

Kansas City, MO 64153

Reorder # 1-800-421-1905

Made in U.S.A.

4406 - A0916

HAZARD RATING

4-EXTREME

3-HIGH

2-MODERATE

1-SLIGHT

0-INSIGNIFICANT

HEALTH 3

FIRE 0

INSTABILITY 0

NPE FREE Formula

4406

NDC # 33392-319

KEEP OUT OF REACH OF CHILDREN

! DANGER

MANTENER FUERA DEL ALCANCE DE LOS NINOS

! PELEGRO

WARNINGS AND PRECAUTIONS

Consult Safety Data Sheet Before Using

HAZARD STATEMENTS:

Causes severe skin and eye damage. May be corrosive to metals. Avoid contact with skin and eyes. Wear protective apron, gloves, and goggles or face shield when handling this product. Wash thoroughly after handling this product. Harmful if swallowed. Swallowing product will cause severe burns to lining of throat and stomach.

DIRECTIONS FOR USE:

Manufacturing instruction must be developed by the formulator prior to use of this product.

Note to formulator: Mix well in drum before sampling and before each use. Avoid contact with soft metals.

GDC-28TM Concentrate will flow and mix more easily if a day or prior to formulating it is gradually warmed to 70^0F - 100^0F and then slowly added in a thin stream while mixing.

GDC-28TM Concentrate is an iodophor concentrate based on iodine and glycerin. It is specially formulated as a base for manufacturing topical iodine products.

GDC-28TM Concentrate contains no phosphates.

GDC-28TM Concentrate may be used to manufacture topical animal health care products and related antimicrobials. GDC-28TM Concentrate is not intended for use as a component of iodophor-based sanitizers and disinfectants. It is the responsibility of the distributor of topical antimicrobials to obtain any necessary regulatory approval from the Food and Drug Administration for products formulated from GDC-28TM Concentrate which carry specific label directions for treatment or prevention of animal diseases.

WARNINGS AND PRECAUTIONS

UN1760

Corrosive liquid, NOS, (Iodine Complex) Liquido corrosivo N.E.P. (Contiene Yodo)

NET CONTENTS:

LOT NO:

EXPIRATION DATE: